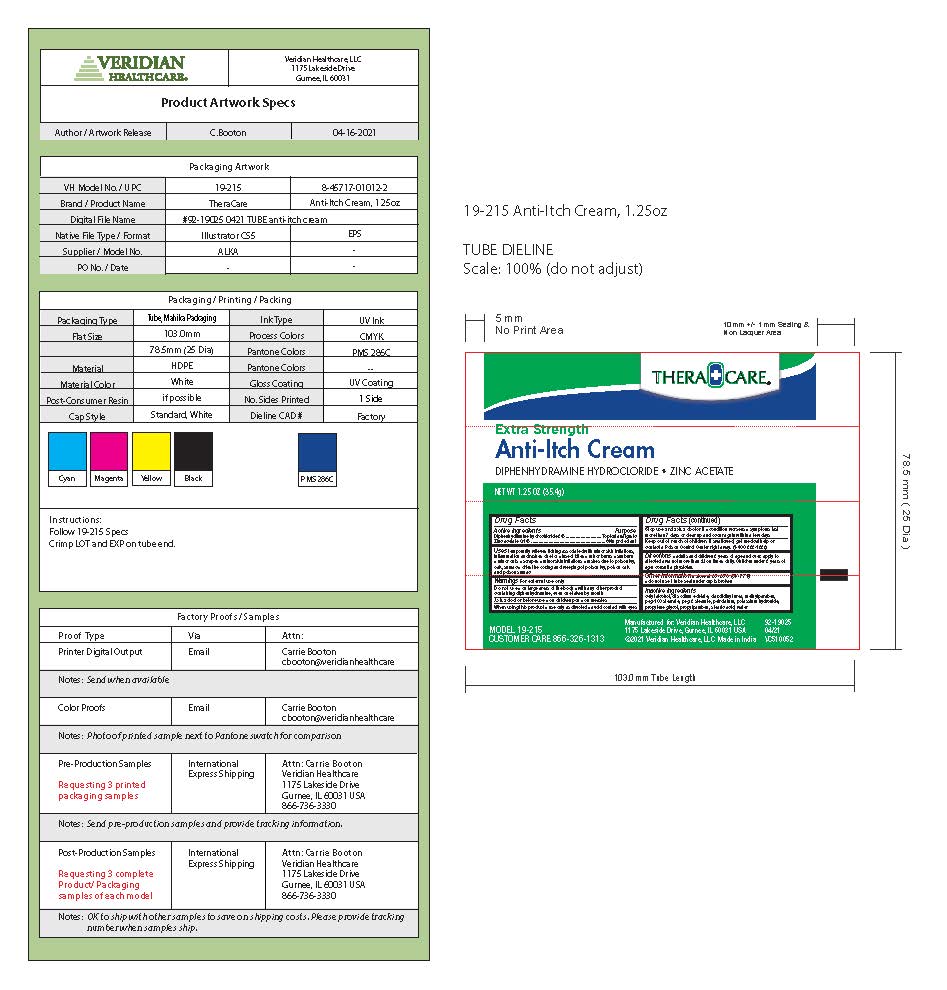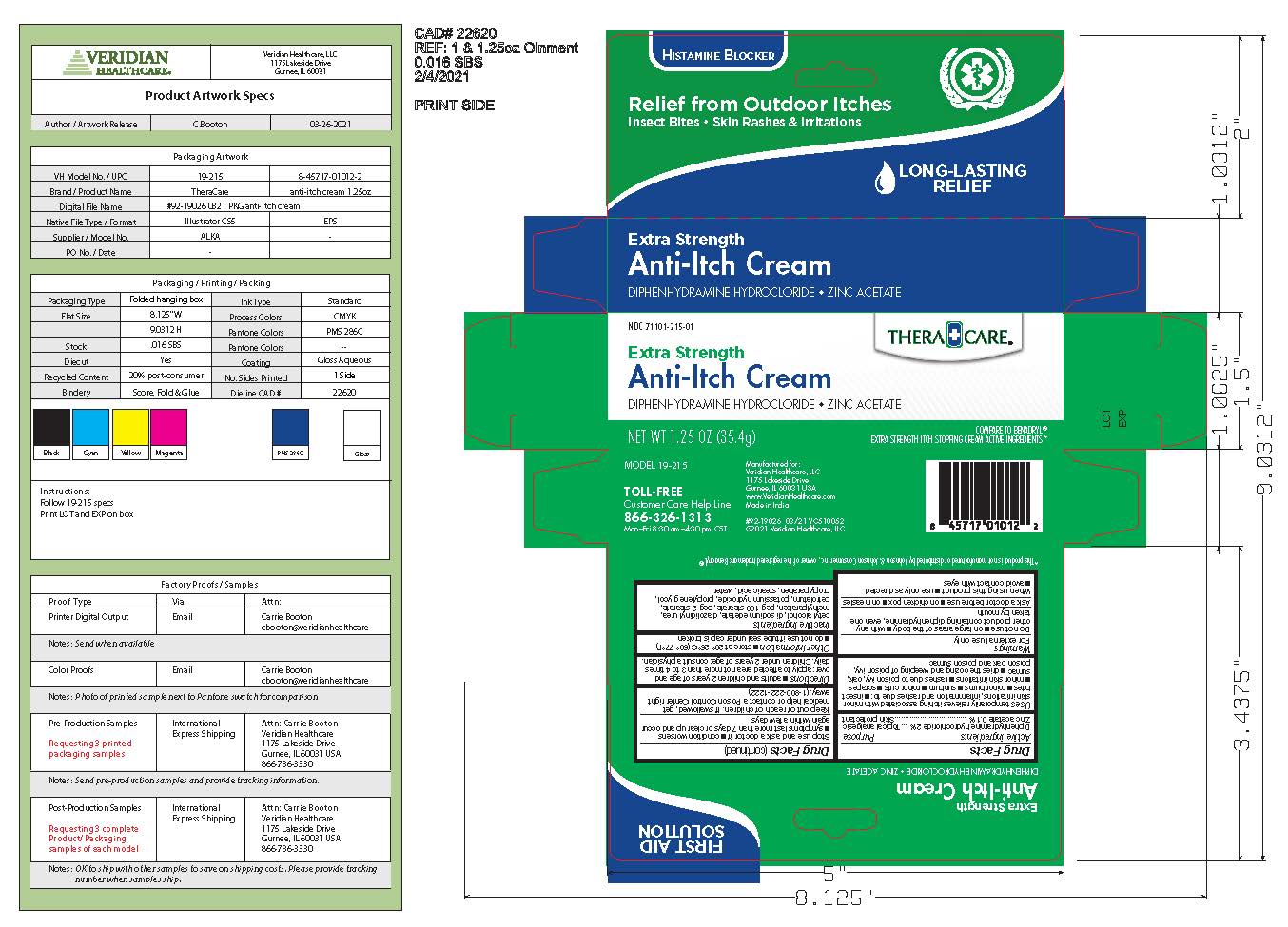 DRUG LABEL: TheraCare Extra Strength Anti-Itch Cream
NDC: 71101-215 | Form: CREAM
Manufacturer: Veridian Healthcare
Category: otc | Type: HUMAN OTC DRUG LABEL
Date: 20241218

ACTIVE INGREDIENTS: DIPHENHYDRAMINE HYDROCHLORIDE 20 mg/1 g; ZINC ACETATE 1 mg/1 g
INACTIVE INGREDIENTS: EDETATE SODIUM; PEG-2 STEARATE; STEARIC ACID; METHYLPARABEN; PETROLATUM; POLYOXYL 100 STEARATE; POTASSIUM HYDROXIDE; CETYL ALCOHOL; DIAZOLIDINYL UREA; PROPYLENE GLYCOL; PROPYLPARABEN; WATER

TheraCare Extra Strength Anti-Itch Cream

Drug Facts

ACTIVE INGREDIENT

Active ingredients | Purpose
Diphenhydramine hydrochloride 2% | Topical analgesic
Zinc acetate 0.1% | Skin protectant

Uses

- temporarily relieves pain and itching associated with:
  - insect bites
  - minor burns
  - sunburn
  - minor skin irritations
  - minor cuts
  - scrapes
  - minor skin irritations
  - rashes due to poison ivy, poison oak, oak, and sumac
- dries the oozing and weeping of poison ivy, poison oak, and poison sumac

Warnings

For external use only

Do not use

- on large areas of the body
- with any other product containing diphenhydramine, even one taken by mouth

Ask a doctor before use

- on chicken pox
- on measles

When using this product

- use only as directed
- avoid contact with eyes

Stop use and ask a doctor if

- condition worsens or does not improve within 7 days
- symptoms persist for more than 7 days or clear up and occur again within a few days

Keep out of reach of children. If swallowed, get medical help or contact a Poison Control Center right away. (1-800-222-1222)

Directions

- adults and children 2 years of age and over: apply to affected area not more than 3 to 4 times daily
- children under 2 years of age: consult a physician

Other information

- store at 20°C-25°C (68°C/77°F)
- do not use if tube seal under cap is broken

Inactive ingredients

cetyl alcohol, di sodium edetate, Diazolidinyl urea, methylparaben, peg-100 stearate, peg-2 stearate, petrolatum, potassium hydroxide, polyethylene glycol, propylparaben, stearic acid, water

Questions?

toll-free 866-326-1313